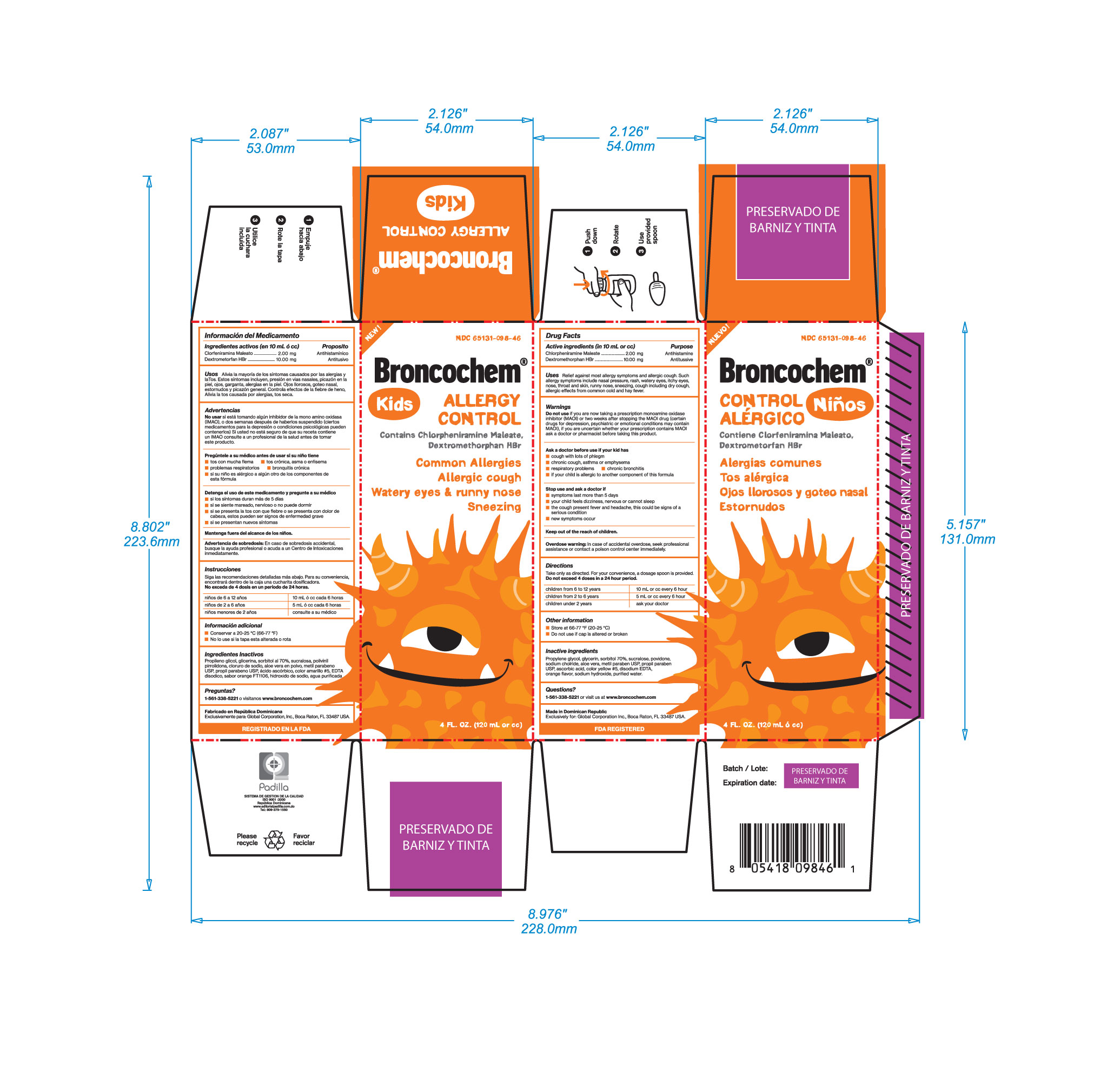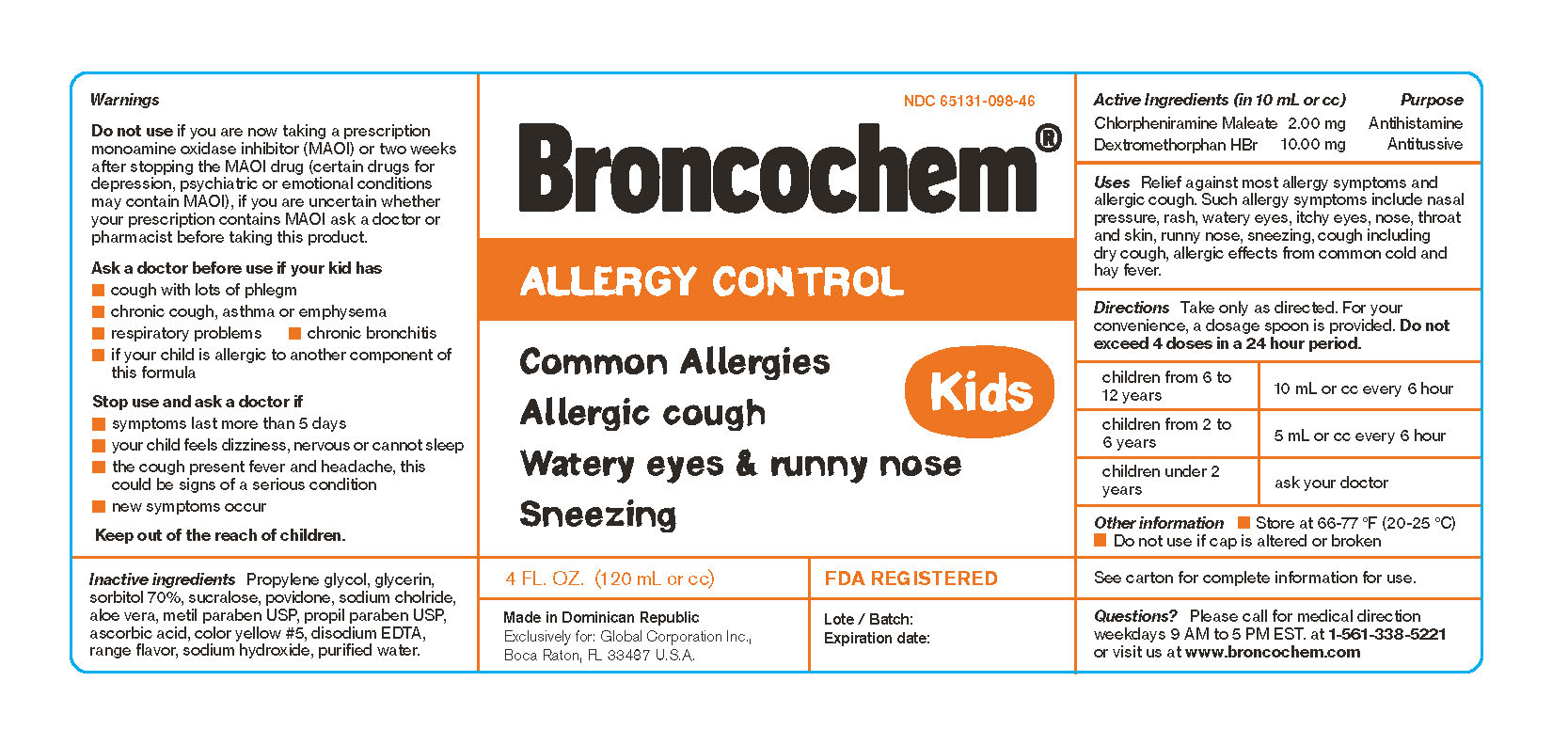 DRUG LABEL: BRONCOCHEM
NDC: 65131-418 | Form: SYRUP
Manufacturer: LABORATORIO MAGANCEHM INTERNATIONAL SRL
Category: otc | Type: HUMAN OTC DRUG LABEL
Date: 20170410

ACTIVE INGREDIENTS: CHLORPHENIRAMINE MALEATE 2 mg/10 mL; DEXTROMETHORPHAN HYDROBROMIDE 10 mg/10 mL
INACTIVE INGREDIENTS: PROPYLENE GLYCOL 1.5 mL/10 mL; GLYCERIN 2 mL/10 mL; SORBITOL 2 mL/10 mL; SUCRALOSE 8.33 mg/10 mL; POVIDONE K90 100 mg/10 mL; SODIUM CHLORIDE 6.25 mg/10 mL; ALOE VERA LEAF 4 mg/10 mL; METHYLPARABEN 10 mg/10 mL; PROPYLPARABEN 1.5 mg/10 mL; ASCORBIC ACID 66 mg/10 mL; FD&C YELLOW NO. 5 0.5 mg/10 mL; DISODIUM HEDTA 0.9 mg/10 mL; ORANGE 0.0016 mg/10 mL; SODIUM HYDROXIDE 13.33 mg/10 mL; WATER 10 mL/10 mL

BRONCOCHEM KIDS ALLERGY CONTROL

Warnings

Do not use

If you are now taking a prescription monoamine oxidase inhibitor (MAOI) or two weks after stopping the MAOI drug (certain drugs for depression, psuchiatric or emotional conditions may contain MAOI), if you are uncertain whether your prescription contains MAOI ask a doctor or pharmacist before taking this product

active ingredients

Dextromethorphan HBr.......10.00mg

Chlorpheniramine maleate...2.00mg

Uses

Temporarily relieves cold symptoms, cough, helps loosen phlegm (mucus) and dilute bronchial secretions to make coughs more productive.

Reduces allergic symptoms like runny nose and sneezing, irritated ans watery eyes, Itchy nose, Itchy throat, Allergy rhinitis

Ask a doctor before use if your kid have

Cough with lots of phlegm

Chornic cough, asthma or emphysema

Respiratory problems

Chornic bronchitis

If your child is allergyc to another component of this formula

Stop use and ask a doctor if

Symptoms last more than 5 days

If your child feels dizziness, nervous or cannot sleep

If the cough present fever and headache, this could be signs of a serious conditions

If new symptoms occur

Keep out of the reach of children

Overdose warning

in case of accidental overdose, seek professional assistance or contact a poison control center immediately

Directions

Take only as directed, for your convenience a dosage spoon is provided

Do not exceed 4 doses in a 24-hour period

Children from 6 to 12 years-----10mL or cc every 6 hours

Children fron 2 to 6 years-------5mL or cc every 6 hours

Children under 2 years, ask your doctor

Other information

Store at 66-77*F (20-25*C), do not use if security cap is altered or broken

Inactive Ingredients

Propylene glycol, Gliceryn, Sorbitol 70%, Sucralose, Povidone, Sodium Chloride, Aloe vera, Methylparaben USP, Propylparaben USP, Ascorbic acid, Color Yellow #5, Dosodium Hedta, Orange flavor, Sodium hydroxide, Purified water

Quiestions?

1-561-338-5221 or visit us at www.broncochem.com

Purpose

Dextromethorphan HBr------Antitussive

Chlorpheniramine maleate--Antihistamine